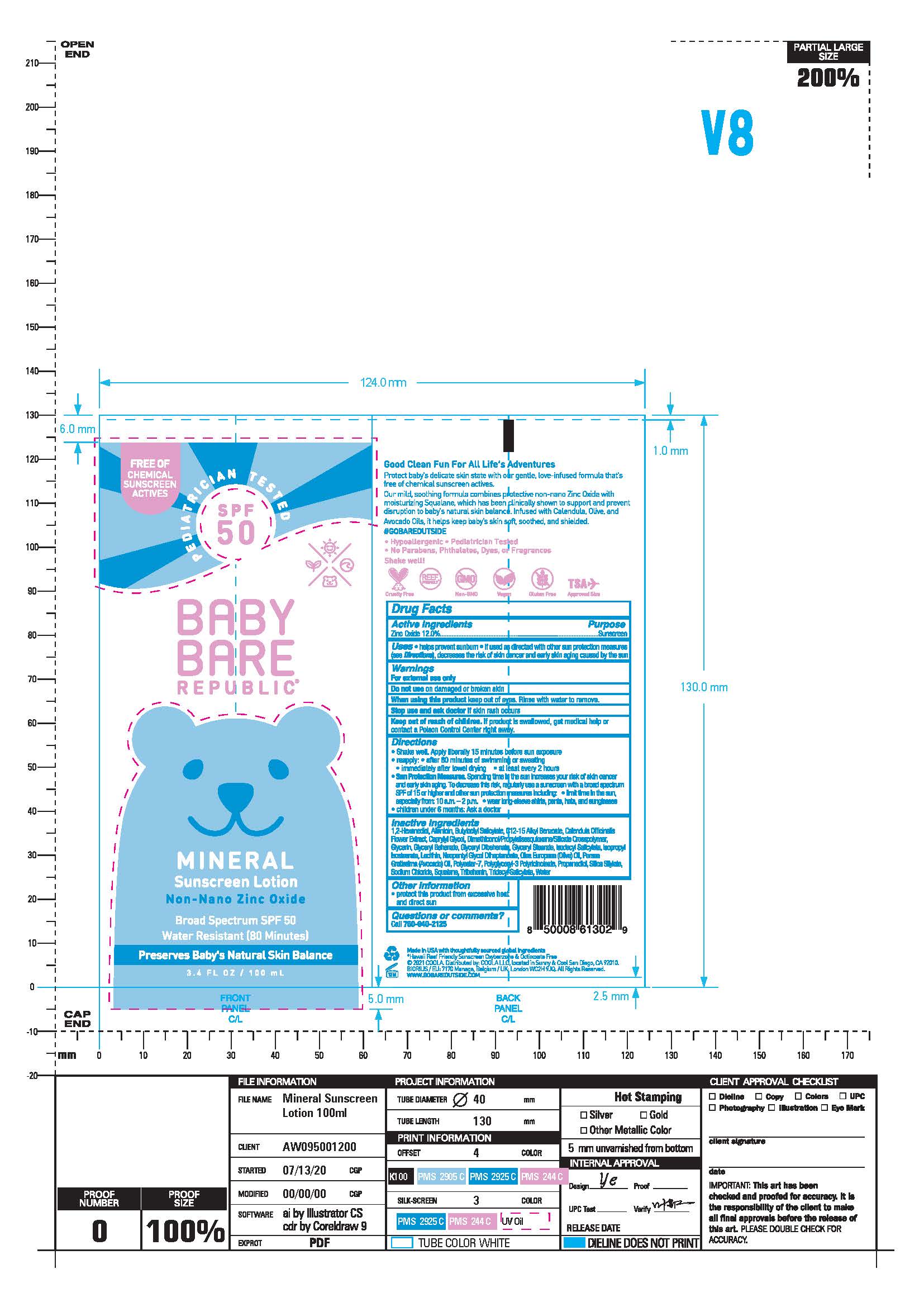 DRUG LABEL: Baby Bare Republic Mineral Sunscreen
NDC: 79753-007 | Form: LOTION
Manufacturer: COOLA, LLC
Category: otc | Type: HUMAN OTC DRUG LABEL
Date: 20251114

ACTIVE INGREDIENTS: ZINC OXIDE 12 mg/1 mL
INACTIVE INGREDIENTS: PROPANEDIOL; WATER; POLYGLYCERYL-3 RICINOLEATE; .ALPHA.-BISABOLOL, (-)-EPI-; CAPRYLYL GLYCOL; TRIDECYL SALICYLATE; ALLANTOIN; BUTYLOCTYL SALICYLATE; GLYCERIN; NEOPENTYL GLYCOL DIHEPTANOATE; SODIUM CHLORIDE; POLYESTER-7; GLYCERYL BEHENATE/EICOSADIOATE; LECITHIN, SOYBEAN; ISODECYL SALICYLATE; OLEA EUROPAEA (OLIVE) OIL UNSAPONIFIABLES; ISOPROPYL ISOSTEARATE; 1,2-HEXANEDIOL; ALKYL (C12-15) BENZOATE; DIMETHICONOL/PROPYLSILSESQUIOXANE/SILICATE CROSSPOLYMER (450000000 MW); GLYCERYL DIBEHENATE; ISOSTEARIC ACID; CALENDULA OFFICINALIS FLOWER; ISOPROPYL ALCOHOL; TRIBEHENIN; GLYCERYL STEARATE CITRATE; SQUALANE

Baby Bare Republic Mineral Sunscreen